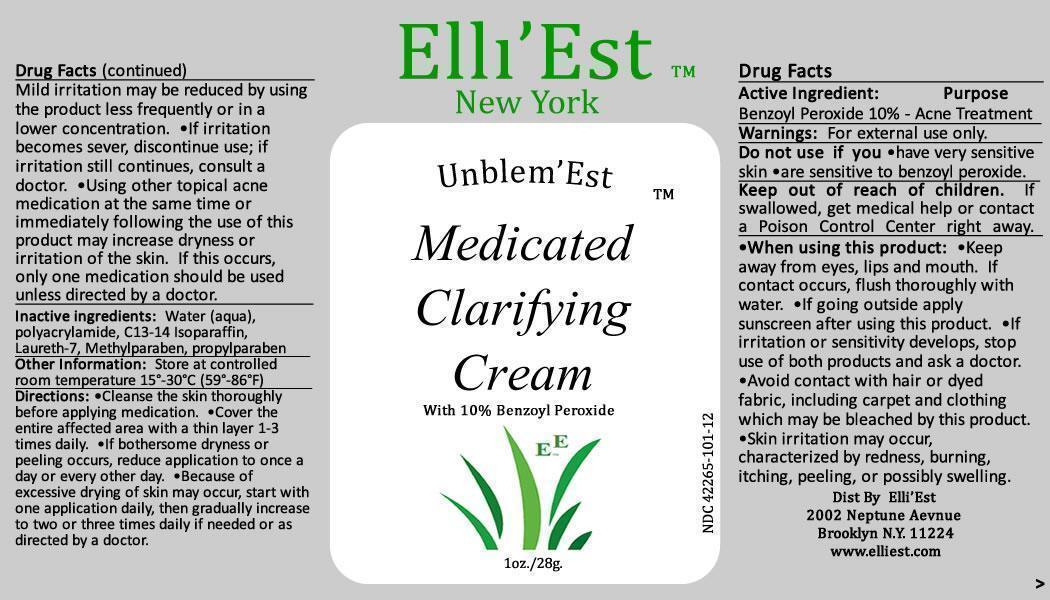 DRUG LABEL: Unblem Est
NDC: 42265-101 | Form: CREAM
Manufacturer: Elli Est
Category: otc | Type: HUMAN OTC DRUG LABEL
Date: 20120921

ACTIVE INGREDIENTS: BENZOYL PEROXIDE 100 mg/1 g
INACTIVE INGREDIENTS: WATER 840 mg/1 g; POLYACRYLAMIDE (CROSSLINKED; 0.01-0.2 MOLE PERCENT BISACRYLAMIDE) 30 mg/1 g; C13-14 ISOPARAFFIN 15 mg/1 g; Laureth-7 10 mg/1 g; Methylparaben 2.5 mg/1 g; Propylparaben 2.5 mg/1 g

Active Ingredients: Benzoyl Peroxide 10%

Purpose: Acne Treatment

Keep out of reach of children: if
swallowed, get medical help or contact
a poison control center right away

Usage: For external use only.
Do not use if: you have very sensitive
skin are sensitive to benzoyl peroxide.

WARNINGS

Warning: For external use only.
Do not use if you- have very sensitive skin-are sensitive to benzoyl peroxide.
Keep 0ut of reach of children. If swallowed, get medical help or contact a poison control center right away.
When using this product -keep away from eyes, lips and mouth.-
If contact occurs, flush thoroughly with water.- If going outside apply sunscreen after using this product.
-If irritation or sensitivity develops, stop use of both products and ask a doctor.
Avoid contact with hair or dyed fabric,including carpet and clothing which may be bleached by this product.
-skin irritation may occur ,characterized by redness, burning , itching, peeling or possibly swelling.
Mild irritation may be reduced by using the product less frequently or in a lower concentration. -If irritation becomes sever, discontinue use.
If irritation still continues ,consult a doctor.
-Using other topical acne medication at the same time or immediately following the use of this product may increase dryness or irritation of the skin.
If this occurs only one medication should be used unless directed by a doctor

DOSAGE AND ADMINISTRATION

Directions: Cleanse the skin thoroughly before applying medication.- Cover the entire affected area with a thin layer 1 to 3 times daily.
-If bothersome dryness or peeling occurs, reduce application to once a day or every other day.
- Because of excessive drying of the skin may occur start with one application daily, then gradually increase to two or three times daily if needed or as
directed by a doctor.

INACTIVE INGREDIENT

Inactive Ingredients: Water (Aqua), Polyacrylamide crosslinked 0.01-0.2 mole percent bisacrlyamid
C-13-14 Isoparafin, laureth-7, Methylparaben, Propylparaben.

PACKAGE LABEL

Elli'Est
Unblem'Est
Medicated Clarifying Lotion
With 10% Benzoyl Peroxide
1oz. / 28g.

ndc42265-101-12
label image
bpo1